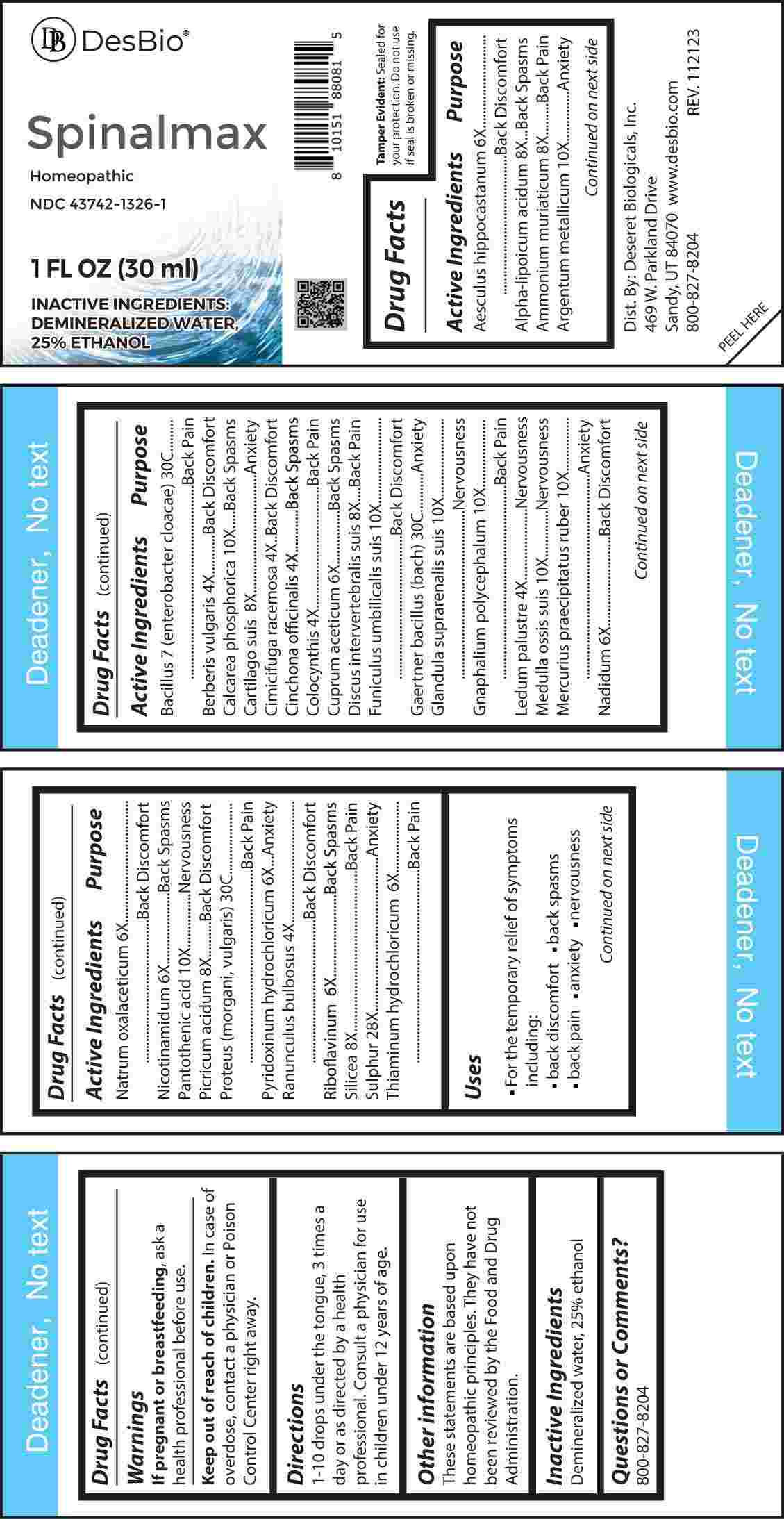 DRUG LABEL: Spinalmax
NDC: 43742-1326 | Form: LIQUID
Manufacturer: Deseret Biologicals, Inc.
Category: homeopathic | Type: HUMAN OTC DRUG LABEL
Date: 20240311

ACTIVE INGREDIENTS: BERBERIS VULGARIS ROOT BARK 4 [hp_X]/1 mL; BLACK COHOSH 4 [hp_X]/1 mL; CINCHONA OFFICINALIS BARK 4 [hp_X]/1 mL; CITRULLUS COLOCYNTHIS FRUIT PULP 4 [hp_X]/1 mL; RHODODENDRON TOMENTOSUM LEAFY TWIG 4 [hp_X]/1 mL; RANUNCULUS BULBOSUS 4 [hp_X]/1 mL; HORSE CHESTNUT 6 [hp_X]/1 mL; CUPRIC ACETATE 6 [hp_X]/1 mL; NADIDE 6 [hp_X]/1 mL; SODIUM DIETHYL OXALACETATE 6 [hp_X]/1 mL; NIACINAMIDE 6 [hp_X]/1 mL; PYRIDOXINE HYDROCHLORIDE 6 [hp_X]/1 mL; RIBOFLAVIN 6 [hp_X]/1 mL; THIAMINE HYDROCHLORIDE 6 [hp_X]/1 mL; ALPHA LIPOIC ACID 8 [hp_X]/1 mL; AMMONIUM CHLORIDE 8 [hp_X]/1 mL; SUS SCROFA CARTILAGE 8 [hp_X]/1 mL; SUS SCROFA INTERVERTEBRAL DISC 8 [hp_X]/1 mL; PICRIC ACID 8 [hp_X]/1 mL; SILICON DIOXIDE 8 [hp_X]/1 mL; SILVER 10 [hp_X]/1 mL; TRIBASIC CALCIUM PHOSPHATE 10 [hp_X]/1 mL; SUS SCROFA UMBILICAL CORD 10 [hp_X]/1 mL; SUS SCROFA ADRENAL GLAND 10 [hp_X]/1 mL; PSEUDOGNAPHALIUM OBTUSIFOLIUM WHOLE 10 [hp_X]/1 mL; SUS SCROFA BONE MARROW 10 [hp_X]/1 mL; MERCURIC OXIDE 10 [hp_X]/1 mL; PANTOTHENIC ACID 10 [hp_X]/1 mL; SULFUR 28 [hp_X]/1 mL; ENTEROBACTER CLOACAE 30 [hp_C]/1 mL; SALMONELLA ENTERICA SUBSP. ENTERICA SEROVAR ENTERITIDIS 30 [hp_C]/1 mL; PROTEUS MORGANII 30 [hp_C]/1 mL; PROTEUS VULGARIS 30 [hp_C]/1 mL
INACTIVE INGREDIENTS: WATER; ALCOHOL

DRUG FACTS:

ACTIVE INGREDIENTS:

Aesculus Hippocastanum 6X, Alpha-Lipoicum Acidum 8X, Ammonium Muriaticum 8X, Argentum Metallicum 10X, Bacillus 7 (enterobacter cloacae) 30C, Berberis Vulgaris 4X, Calcarea Phosphorica 10X, Cartilago Suis 8X, Cimicifuga Racemosa 4X, Cinchona Officinalis 4X, Colocynthis 4X, Cuprum Aceticum 6X, Discus Intervertebralis Suis 8X, Funiculus Umbilicalis Suis 10X, Gaertner Bacillus (Bach) 30C, Glandula Suprarenalis Suis 10X, Gnaphalium Polycephalum 10X, Ledum Palustre 4X, Medulla Ossis Suis 10X, Mercurius Praecipitatus Ruber 10X, Nadidum 6X, Natrum Oxalaceticum 6X, Nicotinamidum 6X, Pantothenic Acid 10X, Picricum Acidum 8X, Proteus (Morgani, Vulgaris) 30C, Pyridoxinum Hydrochloricum 6X, Ranunculus Bulbosus 4X, Riboflavinum 6X, Silicea 8X, Sulphur 28X, Thiaminum Hydrochloricum 6X.

PURPOSE:

Aesculus Hippocastanum – Back Discomfort, Alpha-Lipoicum Acidum – Back Spasms, Ammonium Muriaticum – Back Pain, Argentum Metallicum - Anxiety, Bacillus 7 (Enterobacter Cloacae) – Back Pain, Berberis Vulgaris – Back Discomfort, Calcarea Phosphorica – Back Spasms, Cartilago Suis - Anxiety, Cimicifuga Racemosa – Back Discomfort, Cinchona Officinalis – Back Spasms, Colocynthis – Back Pain, Cuprum Aceticum – Back Spasms, Discus Intervertebralis Suis – Back Pain, Funiculus Umbilicalis Suis – Back Discomfort, Gaertner Bacillus (Bach) - Anxiety, Glandula Suprarenalis Suis - Nervousness, Gnaphalium Polycephalum – Back Pain, Ledum Palustre - Nervousness, Medulla Ossis Suis - Nervousness, Mercurius Praecipitatus Ruber - Anxiety, Nadidum – Back Discomfort, Natrum Oxalaceticum – Back Discomfort, Nicotinamidum – Back Spasms, Pantothenic Acid – Nervousness, Picricum Acidum – Back Discomfort, Proteus (Morgani, Vulgaris) – Back Pain, Pyridoxinum Hydrochloricum - Anxiety, Ranunculus Bulbosus – Back Discomfort, Riboflavinum – Back Spasms, Silicea – Back Pain, Sulphur – Anxiety, Thiaminum Hydrochloricum – Back Pain

INDICATION:

• For the temporary relief of symptoms including:

• back discomfort • back spasms

• back pain • anxiety • nervousness

These statements are based upon homeopathic principles. They have not been reviewed by the Food and Drug Administration.

WARNINGS:

If pregnant or breast-feeding, ask a health professional before use.

Keep out of reach of children. In case of overdose, contact a physician or Poison Control Center right away.

Tamper Evident: Sealed for your protection. Do not use if seal is broken or missing.

KEEP OUT OF REACH OF CHILDREN:

In case of overdose, contact a physician or Poison Control Center right away.

DIRECTIONS:

1-10 drops under the tongue, 3 times a day or as directed by a health professional. Consult a physician for use in children under 12 years of age.

INACTIVE INGREDIENTS:

Demineralized water, 25% ethanol

QUESTIONS:

Dist. By: Deseret Biologicals, Inc.
469 W. Parkland Drive
Sandy, UT 84070

www.desbio.com

800-827-8204

PACKAGE LABEL DISPLAY:

Des Bio

Spinalmax

Homeopathic

NDC 43742-1326-1

1 FL OZ (30 ml)